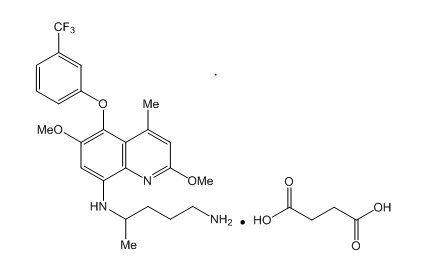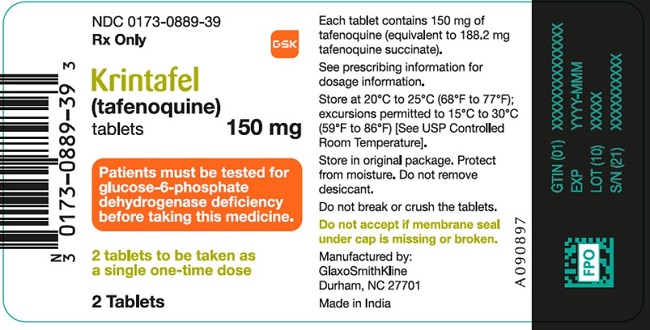 DRUG LABEL: Krintafel
NDC: 0173-0889 | Form: TABLET, FILM COATED
Manufacturer: GlaxoSmithKline LLC
Category: prescription | Type: HUMAN PRESCRIPTION DRUG LABEL
Date: 20230802

ACTIVE INGREDIENTS: TAFENOQUINE SUCCINATE 150 mg/1 1
INACTIVE INGREDIENTS: MAGNESIUM STEARATE; MANNITOL; MICROCRYSTALLINE CELLULOSE; HYPROMELLOSE, UNSPECIFIED; POLYETHYLENE GLYCOL, UNSPECIFIED; FERRIC OXIDE RED; TITANIUM DIOXIDE

HIGHLIGHTS OF PRESCRIBING INFORMATION

These highlights do not include all the information needed to use KRINTAFEL safely and effectively. See full prescribing information for KRINTAFEL.
KRINTAFEL (tafenoquine) tablets, for oral use
Initial U.S. Approval: 2018

1 INDICATIONS AND USAGE

KRINTAFEL is an antimalarial indicated for the radical cure (prevention of relapse) of Plasmodium vivax malaria in patients aged 16 years and older who are receiving chloroquine therapy for acute P. vivax infection. (1)

Limitations of Use

- KRINTAFEL is NOT indicated for the treatment of acute P. vivax malaria. (1)
- The concomitant use of KRINTAFEL with antimalarials other than chloroquine is not recommended because of the risk of recurrence of P. vivax malaria. (1, 5.6)

2 DOSAGE AND ADMINISTRATION

- All patients must be tested for glucose-6-phosphate dehydrogenase (G6PD) deficiency prior to prescribing KRINTAFEL. (2.1)
- Pregnancy testing is recommended for females of reproductive potential prior to initiating treatment with KRINTAFEL. (2.1)
- The recommended dose of KRINTAFEL in patients aged 16 years and older is a single dose of 300 mg administered as two 150-mg KRINTAFEL tablets taken together. (2.2)
- Coadminister KRINTAFEL on the first or second day of chloroquine therapy for the acute P. vivax malaria. (2.2)
- Administer KRINTAFEL with food. (2.2)

3 DOSAGE FORMS AND STRENGTHS

Tablets: 150 mg of tafenoquine (3)

4 CONTRAINDICATIONS

- G6PD deficiency or unknown G6PD status. (4)
- Breastfeeding by a lactating woman when the infant is found to be G6PD deficient or if G6PD status is unknown. (4, 8.2)
- Known hypersensitivity reactions to tafenoquine, other 8-aminoquinolines, or any component of KRINTAFEL. (4)

5 WARNINGS AND PRECAUTIONS

- Hemolytic Anemia: G6PD testing must be performed before prescribing KRINTAFEL due to the risk of hemolytic anemia. Monitor patients for clinical signs or symptoms of hemolysis. (5.1)
- G6PD Deficiency in Pregnancy or Lactation: KRINTAFEL may cause hemolytic anemia when administered to a pregnant woman with a G6PD-deficient fetus. KRINTAFEL is not recommended during pregnancy. A G6PD-deficient infant may be at risk for hemolytic anemia from exposure to KRINTAFEL through breast milk. Check infant’s G6PD status before breastfeeding begins. (5.2, 8.1, 8.2)
- Methemoglobinemia: Asymptomatic elevations in blood methemoglobin have been observed. Initiate appropriate therapy if signs or symptoms of methemoglobinemia occur. (5.3)
- Psychiatric Effects: Serious psychiatric adverse reactions have been observed in patients with a previous history of psychiatric conditions at doses higher than the approved dose. The benefit of treatment with KRINTAFEL must be weighed against the potential risk for psychiatric adverse reactions in patients with a history of psychiatric illness. (5.4)
- Hypersensitivity Reactions: Serious hypersensitivity reactions (e.g., angioedema) have been observed with administration of KRINTAFEL. If hypersensitivity reactions occur, institute appropriate therapy. (5.5)
- Due to the long half-life of KRINTAFEL (15 days), psychiatric effects and hypersensitivity reactions may be delayed in onset and/or duration. (5.4, 5.5, 12.3)
- Risk of P. vivax Malaria Recurrence: Lack of efficacy in reducing P. vivax malaria recurrence in patients treated with KRINTAFEL combined with dihydroartemisinin/piperaquine (not approved artemisinin-containing antimalarial) was seen in a clinical trial. Use with antimalarials other than chloroquine is not recommended. (1, 5.6)

6 ADVERSE REACTIONS

Common adverse reactions (≥5%) were dizziness, nausea, vomiting, headache, and decreased hemoglobin. (6.1)

To report SUSPECTED ADVERSE REACTIONS, contact GlaxoSmithKline at 1-888-825-5249 or FDA at 1-800-FDA-1088 or www.fda.gov/medwatch.

7 DRUG INTERACTIONS

Avoid coadministration with drugs that are substrates of organic cation transporter-2 (OCT2) or multidrug and toxin extrusion (MATE) transporters. (7.1)

8 USE IN SPECIFIC POPULATIONS

Lactation: Advise women not to breastfeed a G6PD-deficient infant or infant with unknown G6PD status for 3 months after the dose of KRINTAFEL. (8.2)

FULL PRESCRIBING INFORMATION

1 INDICATIONS AND USAGE

KRINTAFEL is indicated for the radical cure (prevention of relapse) of Plasmodium vivax malaria in patients aged 16 years and older who are receiving chloroquine therapy for acute P. vivax infection [see Dosage and Administration (2.2)].

Limitations of Use

- KRINTAFEL is NOT indicated for the treatment of acute P. vivax malaria.
- Concomitant use of KRINTAFEL with antimalarials other than chloroquine is not recommended because of the risk of recurrence of P. vivax malaria [see Warnings and Precautions (5.6)].

2 DOSAGE AND ADMINISTRATION

2.1 Tests to be Performed Prior to Treatment with KRINTAFEL

All patients must be tested for glucose-6-phosphate dehydrogenase (G6PD) deficiency prior to prescribing KRINTAFEL [see Contraindications (4), Warnings and Precautions (5.1)].

Pregnancy testing is recommended for females of reproductive potential prior to initiating treatment with KRINTAFEL [see Use in Specific Populations (8.1, 8.3)].

2.2 Recommended Dosage and Administration

The recommended dose of KRINTAFEL in patients aged 16 years and older is a single dose of 300 mg administered as two 150-mg tablets taken together. Coadminister KRINTAFEL on the first or second day of chloroquine therapy for acute P. vivax malaria [see Clinical Studies (14)].

Administer KRINTAFEL with food to increase systemic absorption [see Clinical Pharmacology (12.3)].

Swallow tablets whole. Do not break, crush, or chew the tablets.

In the event of vomiting within 1 hour after dosing, a repeat dose should be given. Re-dosing should not be attempted more than once.

3 DOSAGE FORMS AND STRENGTHS

KRINTAFEL tablets are pink, film‑coated, capsule-shaped tablets debossed with ‘GS J11’ on one side and contain 150 mg of tafenoquine.

4 CONTRAINDICATIONS

KRINTAFEL is contraindicated in:

- Patients with G6PD deficiency or unknown G6PD status due to the risk of hemolytic anemia [see Warnings and Precautions (5.1)].
- Breastfeeding by a lactating woman when the infant is found to be G6PD deficient or if the G6PD status of the infant is unknown [see Use in Specific Populations (8.2)].
- Patients with known hypersensitivity to tafenoquine, other 8-aminoquinolines, or any component of KRINTAFEL [see Warnings and Precautions (5.5)].

5 WARNINGS AND PRECAUTIONS

5.1 Hemolytic Anemia

Due to the risk of hemolytic anemia in patients with G6PD deficiency, G6PD testing must be performed before prescribing KRINTAFEL [see Dosage and Administration (2.1)]. Due to the limitations of G6PD tests, physicians need to be aware of residual risk of hemolysis and adequate medical support and follow-up to manage hemolytic risk should be available. Treatment with KRINTAFEL is contraindicated in patients with G6PD deficiency or unknown G6PD status [see Contraindications (4)]. Patients were excluded from clinical trials of KRINTAFEL if they had a G6PD enzyme activity level <70% of the site median value for G6PD normal activity [see Clinical Studies (14)]. In clinical trials, declines in hemoglobin levels were reported in some G6PD-normal patients [see Adverse Reactions (6.1)]. Monitor patients for clinical signs or symptoms of hemolysis. Advise patients to seek medical attention if signs of hemolysis occur.

5.2 G6PD Deficiency in Pregnancy or Lactation

Potential Harm to the Fetus

The use of KRINTAFEL during pregnancy may cause hemolytic anemia in a G6PD-deficient fetus. Even if a pregnant woman has normal levels of G6PD, the fetus could be G6PD deficient. Advise females of reproductive potential that treatment with KRINTAFEL during pregnancy is not recommended and to avoid pregnancy or use effective contraception for 3 months after the dose of KRINTAFEL [see Use in Specific Populations (8.1, 8.3)].

Potential Harm to the Breastfeeding Infant

A G6PD-deficient infant may be at risk for hemolytic anemia from exposure to KRINTAFEL through breast milk. Infant G6PD status should be checked before breastfeeding begins. KRINTAFEL is contraindicated in breastfeeding women when the infant is found to be G6PD deficient or the G6PD status of the infant is unknown [see Contraindications (4)]. Advise the woman with a G6PD-deficient infant or if the G6PD status of the infant is unknown not to breastfeed for 3 months after the dose of KRINTAFEL [see Use in Specific Populations (8.2)].

5.3 Methemoglobinemia

Asymptomatic elevations in methemoglobin have been observed in the clinical trials of KRINTAFEL [see Adverse Reactions (6.1)]. Institute appropriate therapy if signs or symptoms of methemoglobinemia occur. Carefully monitor individuals with nicotinamide adenine dinucleotide (NADH)-dependent methemoglobin reductase deficiency. Advise patients to seek medical attention if signs of methemoglobinemia occur.

5.4 Psychiatric Effects

Psychiatric adverse reactions including anxiety (<1%), abnormal dreams (<1%), and insomnia (3%) have been reported in clinical trials of KRINTAFEL [see Adverse Reactions (6.1)]. Two cases of depression and 2 cases of psychosis have occurred primarily in patients with a history of psychiatric disorders following receipt of single doses of tafenoquine that were higher than the approved 300-mg dose (350 mg to 600 mg). Safety and effectiveness of KRINTAFEL have not been established at doses or regimens other than the approved regimen; use of KRINTAFEL at doses or regimens other than a 300-mg single dose is not approved by FDA.

The benefit of treatment with KRINTAFEL must be weighed against the potential risk for psychiatric adverse reactions in patients with a history of psychiatric illness. Due to the long half-life of KRINTAFEL (approximately 15 days), signs or symptoms of psychiatric adverse reactions that may occur could be delayed in onset and/or duration [see Clinical Pharmacology (12.3)].

5.5 Hypersensitivity Reactions

Serious hypersensitivity reactions (e.g., angioedema, urticaria) have been observed with administration of KRINTAFEL [see Adverse Reactions (6.1)]. Institute appropriate therapy if hypersensitivity reactions occur. Do not re-administer KRINTAFEL. KRINTAFEL is contraindicated in patients who develop hypersensitivity to tafenoquine or any component of KRINTAFEL or other 8-aminoquinolines [see Contraindications (4)].

Due to the long half-life of KRINTAFEL (approximately 15 days), signs or symptoms of hypersensitivity adverse reactions that may occur could be delayed in onset and/or duration [see Clinical Pharmacology (12.3)]. Advise patients to seek medical attention if signs of hypersensitivity occur.

5.6 Risk of P. vivax Malaria Recurrence

Lack of efficacy in reducing P. vivax malaria recurrence in patients treated with KRINTAFEL combined with an artemisinin-containing antimalarial was seen in a clinical trial (NCT02802501). In this double-blind, randomized, placebo-controlled trial in which all patients with P. vivax malaria were treated with dihydroartemisinin/piperaquine (not approved artemisinin-containing antimalarial) and were coadministered KRINTAFEL, primaquine, or placebo, lack of efficacy (recurrence rates at 6 months following treatment) was seen in patients treated with KRINTAFEL.

Concomitant administration of KRINTAFEL with antimalarials other than chloroquine is not recommended.

6 ADVERSE REACTIONS

The following clinically significant adverse reactions have been observed with KRINTAFEL and are discussed in detail in the Warnings and Precautions section:

- Hemolytic anemia [see Warnings and Precautions (5.1)]
- Methemoglobinemia [see Warnings and Precautions (5.3)]
- Psychiatric effects [see Warnings and Precautions (5.4)]
- Hypersensitivity reactions [see Warnings and Precautions (5.5)]

6.1 Clinical Trials Experience

Because clinical trials are conducted under widely varying conditions, adverse reaction rates observed in the clinical trials of a drug cannot be directly compared with rates in the clinical trials of another drug and may not reflect the rates observed in practice.

The safety data described below reflect exposure to 4,129 subjects, of whom 810 received a 300-mg single dose of KRINTAFEL. KRINTAFEL was evaluated in patients with P. vivax malaria (n = 483) in 3 randomized, double-blind trials including a placebo-controlled trial comparing KRINTAFEL plus chloroquine (n = 260) with chloroquine alone (Trial 1), a placebo-controlled dose-ranging trial (Trial 2) (n = 57) [see Clinical Studies (14)], and a hematologic safety trial (Trial 3, NCT02216123) (n = 166).

In Trial 1, in patients with P. vivax malaria, the most common adverse reactions reported in ≥5% of patients treated with KRINTAFEL are listed in Table 1. Patients included in the trial had a mean age of 35 (range: 16 to 79 years), were 75% male and from the following regions: 70% Latin America (Brazil and Peru), 19% Southeast (SE) Asia (Thailand, Cambodia, and the Philippines), and 11% Africa (Ethiopia).

Table 1. Selected Adverse Reactionsa Reported in ≥5% of Patients with P. vivax Malaria Receiving KRINTAFEL in a Randomized, Active-Controlled Trial (Trial 1)
Adverse Reaction | Chloroquine | KRINTAFEL; + Chloroquine
Adverse Reaction | (n = 133) | (n = 260)
Adverse Reaction | % | %
Dizziness | 3 | 8
Nausea | 7 | 6
Vomiting | 5 | 6
Decreased Hemoglobin | 2 | 5
Headache | 7 | 5
a Adverse reactions reported prior to Day 29 as subsequent adverse reactions can be confounded by recurrence of malaria or retreatment with another agent from the quinoline class.

Other Adverse Reactions Reported with KRINTAFEL

Clinically significant adverse reactions with KRINTAFEL 300-mg single dose in clinical trials (n = 810) in ≤3% of subjects are listed below:

Psychiatric Disorders: Anxiety, insomnia, abnormal dreams.

Nervous System Disorders: Somnolence.

Laboratory Investigations: Increased blood creatinine, increased blood methemoglobin, increased alanine aminotransferase.

Immune System Disorders: Hypersensitivity reactions (e.g., angioedema, urticaria) [see Contraindications (4), Warnings and Precautions (5.5)].

Eye Disorders: Vortex keratopathy, photophobia.

7 DRUG INTERACTIONS

7.1 Effect of KRINTAFEL on Organic Cation Transporter-2 (OCT2) and Multidrug and Toxin Extrusion (MATE) Substrates

The effect of coadministration of tafenoquine on the pharmacokinetics of OCT2 and MATE substrates in humans is unknown. However, in vitro observations suggest the potential for increased concentrations of these substrates [see Clinical Pharmacology (12.3)] which may increase the risk of toxicity of these drugs.

Avoid coadministration of KRINTAFEL with OCT2 and MATE substrates (e.g., dofetilide, metformin). If coadministration cannot be avoided, monitor for drug-related toxicities and consider dosage reduction if needed based on approved product labeling of the coadministered drug.

8 USE IN SPECIFIC POPULATIONS

8.1 Pregnancy

Risk Summary

The use of KRINTAFEL during pregnancy may cause hemolytic anemia in a fetus who is G6PD deficient. Treatment with KRINTAFEL during pregnancy is not recommended [see Warnings and Precautions (5.2)]. Available data with use of KRINTAFEL in pregnant women are insufficient to establish a drug-associated risk of major birth defects, miscarriage, or adverse maternal or fetal outcomes. In animal studies, there were increased abortions, with and without maternal toxicity, when KRINTAFEL was given orally to pregnant rabbits at and above doses equivalent to about 0.4 times the clinical exposure based on body surface area comparisons. No fetotoxicity was observed at doses equivalent to the clinical exposure (based on body surface area comparisons) in a similar study in rats.

The estimated background risk of major birth defects and miscarriage for the indicated population is unknown. All pregnancies have a background risk of birth defect, loss, or other adverse outcomes. In the U.S. general population, the estimated background risk of major birth defects and miscarriage in clinically recognized pregnancies is 2% to 4% and 15% to 20%, respectively.

Clinical Considerations

Disease-Associated Maternal and/or Embryo/Fetal Risk: Malaria during pregnancy increases the risk for adverse pregnancy outcomes, including maternal anemia, prematurity, spontaneous abortion, and stillbirth.

Data

Animal Data: Tafenoquine resulted in dose-related abortions when given orally to pregnant rabbits during organogenesis (Gestation Days 6 to 18) at doses of 7 mg/kg (about 0.4 times the clinical exposure based on body surface area comparisons) and above. Doses higher than 7 mg/kg were also associated with maternal toxicity (mortality and reduced body weight gain). In a similar study in rats, doses of 3, 10, or 30 mg/kg/day resulted in maternal toxicity (enlarged spleen, reduced body weight, and reduced food intake) but no fetotoxicity at the high dose (equivalent to the clinical exposure based on body surface area comparisons). There was no evidence of malformations in either species. In a pre- and postnatal development study in rats, tafenoquine administered throughout pregnancy and lactation produced maternal toxicity and a reversible decrease in offspring body weight gain and decrease in motor activity at 18 mg/kg/day, which is equivalent to about 0.6 times the clinical dose based on body surface area comparisons.

8.2 Lactation

Risk Summary

A breastfed infant with G6PD deficiency is at risk for hemolytic anemia from exposure to KRINTAFEL. Infant G6PD status should be checked before breastfeeding begins. KRINTAFEL is contraindicated in breastfeeding women when the infant is found to be G6PD deficient or the G6PD status of the infant is unknown [see Contraindications (4), Clinical Considerations].

There is no information regarding the presence of KRINTAFEL in human milk, the effects of the drug on the breastfed infant, or the effects of the drug on milk production. In a breastfed infant with normal G6PD, the developmental and health benefits of breastfeeding should be considered along with the mother’s clinical need for KRINTAFEL and any potential effects on the breastfed infant from KRINTAFEL or from the underlying maternal condition.

Clinical Considerations

Check the infant’s G6PD status before maternal breastfeeding commences. If an infant is G6PD deficient, exposure to KRINTAFEL during breastfeeding may result in hemolytic anemia in the infant; therefore, advise the woman with an infant who has G6PD deficiency or whose G6PD status is unknown not to breastfeed for 3 months after the dose of KRINTAFEL.

8.3 Females and Males of Reproductive Potential

Pregnancy Testing

Verify the pregnancy status in females of reproductive potential prior to initiating treatment with KRINTAFEL [see Warnings and Precautions (5.2), Use in Specific Populations (8.1)].

Contraception

KRINTAFEL may cause hemolytic anemia in a G6PD-deficient fetus [see Warnings and Precautions (5.2), Use in Specific Populations (8.1)]. Advise females of reproductive potential that treatment with KRINTAFEL during pregnancy is not recommended and to avoid pregnancy or use effective contraception for 3 months after the dose of KRINTAFEL.

8.4 Pediatric Use

The safety and effectiveness of KRINTAFEL have been established in pediatric patients aged 16 years and older. Use of KRINTAFEL in these pediatric patients is supported by evidence from adequate and well-controlled studies of KRINTAFEL [see Clinical Studies (14)].

Safety and effectiveness of KRINTAFEL in pediatric patients younger than 16 years have not been established.

8.5 Geriatric Use

Clinical trials of KRINTAFEL did not include sufficient numbers of patients aged 65 years and older to determine whether they respond differently from younger patients. Other reported clinical experience has not identified differences in responses between the elderly and younger patients [see Clinical Pharmacology (12.3)].

8.6 Renal Impairment

The pharmacokinetics of KRINTAFEL have not been studied in patients with renal impairment. If KRINTAFEL is administered to such patients, monitoring for adverse reactions associated with KRINTAFEL is needed [see Warnings and Precautions (5), Adverse Reactions (6)].

8.7 Hepatic Impairment

The pharmacokinetics of KRINTAFEL have not been studied in patients with hepatic impairment. If KRINTAFEL is administered to such patients, monitoring for adverse reactions associated with KRINTAFEL is needed [see Warnings and Precautions (5), Adverse Reactions (6)].

10 OVERDOSAGE

Hemoglobin decline and methemoglobinemia may be encountered in an overdose with KRINTAFEL. Treatment of overdosage consists of institution of appropriate symptomatic and/or supportive therapy.

11 DESCRIPTION

KRINTAFEL contains tafenoquine succinate, an antimalarial agent for oral administration. The chemical name of tafenoquine succinate is (±) 8-[(4-amino-1-methylbutyl)amino]-2,6-dimethoxy-4‑methyl-5-[3-(trifluoromethyl)phenoxy]quinoline succinate. The molecular formula of tafenoquine succinate is C24H28F3N3O3•C4H6O4, and its molecular mass is 581.6 as the succinate salt (463.5 as free base). The structural formula is shown below.

Each KRINTAFEL tablet contains 150 mg of tafenoquine (equivalent to 188.2 mg tafenoquine succinate). Inactive ingredients include magnesium stearate, mannitol, and microcrystalline cellulose. The tablet film-coating inactive ingredients include hydroxypropylmethylcellulose, polyethylene glycol, red iron oxide, and titanium dioxide.

12 CLINICAL PHARMACOLOGY

12.1 Mechanism of Action

Tafenoquine is an 8-aminoquinoline antimalarial drug [see Microbiology (12.4)].

12.2 Pharmacodynamics

Cardiac Electrophysiology

The effect of tafenoquine on the QTc interval was evaluated in a Phase 1 randomized, single-blind, placebo- and positive-controlled, parallel-group thorough QTc study in 260 healthy adult subjects. At a cumulative dose of 1,200 mg (400 mg/day for 3 days; 4 times the maximum recommended dose), tafenoquine did not prolong the QTc interval to any clinically relevant extent.

Exposure-Response Relationships

A saturable relationship between tafenoquine exposure (AUC) and clinical response (recurrence-free rate at 6 months) was identified. Tafenoquine exposures achieved with doses of 300 mg and higher are on the plateau of the exposure-response curve. Use of KRINTAFEL at doses or regimens other than a 300-mg single dose is not approved by the FDA.

12.3 Pharmacokinetics

Absorption

Maximum plasma concentrations were generally observed 12 to 15 hours following oral administration.

Food Effect: Plasma tafenoquine AUC increased by 41% and Cmax increased by 31% when administered as an investigational capsule formulation with a high-calorie, high-fat meal (approximately 1,000 calories with 15% protein, 25% carbohydrate, and 60% fat) compared with the fasted state.

Distribution

Protein binding of tafenoquine is >99.5%. The apparent oral volume of distribution is ~1,600 L. Following single- and multiple-oral-dose administration, tafenoquine whole blood concentrations were on average 67% higher than corresponding plasma values.

Elimination

The apparent oral clearance of tafenoquine is approximately 3 L/h. The average terminal half-life is approximately 15 days.

Metabolism: Tafenoquine undergoes slow metabolism. Unchanged tafenoquine represented the only notable drug-related component in human plasma after a single oral dose of tafenoquine.

Excretion: The full excretion profile of tafenoquine in humans is unknown. Over a 6-day collection period, renal elimination of unchanged tafenoquine was low.

Specific Populations

Pharmacokinetics of tafenoquine were not significantly impacted by age, sex, ethnicity, and body weight. The effect of renal or hepatic impairment on tafenoquine pharmacokinetics is unknown.

Drug Interaction Studies

Clinical Studies: No clinically significant effects on tafenoquine pharmacokinetics were observed following coadministration with chloroquine, dihydroartemisinin-piperaquine, or artemether-lumefantrine in healthy subjects.

No clinically significant effects on the pharmacokinetics of dihydroartemisinin, piperaquine, artemether, lumefantrine, or substrates of cytochrome P450 isoenzymes (CYP)1A2 (caffeine), CYP2D6 (desipramine), CYP2C8 (chloroquine), CYP2C9 (flurbiprofen), or CYP3A4 (midazolam, chloroquine) were observed following coadministration of tafenoquine in healthy subjects.

In Vitro Studies Where Drug Interaction Potential Was Not Further Evaluated Clinically: Tafenoquine inhibited metformin transport via human OCT2, MATE-1, and MATE2-K transporters. Clinical drug interaction studies with tafenoquine and OCT2 and MATE substrates have not been conducted [see Drug Interactions (7)].

The effect of tafenoquine on substrates of P-glycoprotein (P-gp), breast cancer resistance protein (BCRP), and organic anion transporting polypeptides 1B1/1B3 (OATP1B1/OATP1B3) is unknown.

12.4 Microbiology

Mechanism of Action

Tafenoquine, an 8-aminoquinoline antimalarial, is active against the liver stages including the hypnozoite (dormant stage) of P. vivax. In addition to its effect on the parasite, tafenoquine causes red blood cell shrinkage in vitro. The molecular target of tafenoquine is not known.

Antimicrobial Activity

Tafenoquine is active against pre-erythrocytic (liver) and erythrocytic (asexual) forms as well as gametocytes of P. vivax. The activity of tafenoquine against the pre-erythrocytic liver stages of the parasite prevents the development of the erythrocytic forms of the parasite, which are responsible for relapses in P. vivax malaria [see Clinical Studies (14)].

Resistance

A potential for development of resistance of Plasmodium species to tafenoquine was not evaluated.

13 NONCLINICAL TOXICOLOGY

13.1 Carcinogenesis, Mutagenesis, Impairment of Fertility

Carcinogenesis

Two-year oral carcinogenicity studies were conducted in rats and mice. Renal cell adenomas and carcinomas were increased in male rats at doses of 1 mg/kg/day and above (3 times the clinical exposure based on AUC comparisons). Tafenoquine was not carcinogenic in mice. Given the single-dose administration of KRINTAFEL, these findings may not represent a carcinogenicity risk to humans.

Mutagenesis

Tafenoquine did not cause mutations or chromosomal damage in 2 definitive in vitro tests (bacterial mutation assay and mouse lymphoma L5178Y cell assay) or in an in vivo oral rat micronucleus test.

Impairment of Fertility

In a rat fertility study, tafenoquine was given orally at 1.5, 5, and 15 mg/kg/day (up to about 0.5 times the human dose based on body surface area comparisons) to males for at least 67 days, including 29 days prior to mating, and to females from 15 days prior to mating through early pregnancy. Tafenoquine resulted in reduced number of viable fetuses, implantation sites, and corpora lutea at 15 mg/kg in the presence of maternal toxicity (mortality, piloerection, rough coat, and reduced body weight).

14 CLINICAL STUDIES

Trial 1 (NCT01376167) was a double-blind, controlled clinical trial of 522 adults positive for P. vivax across 3 regions (Asia, Africa, and Latin America). All patients received chloroquine phosphate (600-mg free base on Days 1 and 2 with 300-mg free base on Day 3) to treat the acute infection in addition to either a one-time dose of KRINTAFEL (two 150-mg tablets) on Day 1 or Day 2 (n = 260), an active control (n = 129), or placebo (n = 133) in a 2:1:1 fashion. Patients included in the trial had a mean age of 35 (range: 16 to 79 years), were 75% male and from the following regions: 70% Latin America (Brazil and Peru), 19% SE Asia (Thailand, Cambodia, and the Philippines), and 11% Africa (Ethiopia).

Patients were considered recurrence-free at 6 months if they demonstrated initial parasite clearance, took no antimalarial medications, and were confirmed parasite-free at the 6-month final assessment (i.e., absence of relapse or new infection).

Due to the risk of hemolytic anemia, patients were excluded from the trial if they had a G6PD enzyme activity level <70% of the site median value for G6PD normals (8.2 IU/gHb). In this trial, the minimum G6PD enzyme level of any subject was 5.4 IU/gHb. Patients with severe malaria were excluded from the trial.

The recurrence-free efficacy rates at 6 months among the groups receiving KRINTAFEL and placebo are presented in Table 2. The risk of recurrence for KRINTAFEL plus chloroquine was reduced by 76% compared with placebo plus chloroquine.

Table 2. Recurrence-Free Efficacy Rates of KRINTAFEL in Patients with P. vivax at 6 Months – Trial 1a
 | KRINTAFEL/ | Placebo/
 | Chloroquine | Chloroquine
 | (n = 260) | (n = 133)
Recurrence-free efficacy | 155 (60%) | 35 (26%)
Recurrence | 85 (33%) | 88 (66%)
Missing/indeterminate outcome | 20 (8%) | 10 (8%)
ORb (95% CI) | 0.24 (0.15, 0.38)
P value | <0.001
a All randomized patients were treated and had a positive parasite smear for P. vivax at baseline.
b Odds ratio of the risk of recurrence of KRINTAFEL plus chloroquine versus placebo plus chloroquine using logistic regression model with treatment and region as covariates. Subjects who did not demonstrate initial clearance, took a concomitant medication with antimalarial activity, or who had a missing Day 180 assessment were considered ‘missing/indeterminate’ and were counted as recurrences in the analysis.

In Trial 2 (NCT01376167), a dose-ranging trial with a study design similar to Trial 1, 57 and 54 subjects were randomized to KRINTAFEL 300-mg single dose plus chloroquine (same dose as in Trial 1) and placebo plus chloroquine groups, respectively. KRINTAFEL plus chloroquine demonstrated a statistically significantly higher rate of recurrence-free efficacy at 6 months compared with the placebo plus chloroquine control group (84% versus 39%, with a difference of 45% and 95% CI [29%, 61%]).

16 HOW SUPPLIED/STORAGE AND HANDLING

How Supplied

KRINTAFEL tablets contain 150 mg of tafenoquine (equivalent to 188.2 mg tafenoquine succinate) and are pink, film‑coated, capsule-shaped, and debossed with ‘GS J11’ on one side. KRINTAFEL is supplied as follows:

- Unit Dose Pack of 2 tablets in a bottle with child-resistant closure (NDC 0173-0889-39). Bottles contain a desiccant.

Storage

Store at 20°C to 25°C (68°F to 77°F). Temperature excursions are permitted to 15°C to 30°C (59°F to 86°F) [see USP Controlled Room Temperature].

Store in the original package to protect from moisture. Keep the bottle tightly closed and do not remove the desiccant.

17 PATIENT COUNSELING INFORMATION

Advise the patient to read the FDA-approved patient labeling (Patient Information).

G6PD Testing and Hemolytic Anemia

Inform patients of the need for testing for G6PD deficiency before starting KRINTAFEL. Advise patients of the symptoms of hemolytic anemia and instruct them to seek medical advice promptly if such symptoms occur. Patients should contact their healthcare provider if they develop dark lips or urine as these may be signs of hemolysis or methemoglobinemia [see Warnings and Precautions (5.1)].

Important Administration Instructions

Advise patients to take KRINTAFEL with food to increase absorption [see Dosage and Administration (2)].

Advise patients to swallow the tablet whole and not to break, crush, or chew it.

Potential Harm to the Fetus

Advise females of reproductive potential of the potential risk of KRINTAFEL to a fetus and to inform their healthcare provider of a known or suspected pregnancy [see Warnings and Precautions (5.2), Use in Specific Populations 8.1)].

Advise females of reproductive potential to avoid pregnancy or use effective contraception for 3 months after the dose of KRINTAFEL [see Use in Specific Populations (8.3)].

Lactation

Advise women with a G6PD-deficient infant, or if they do not know the G6PD status of their infant, not to breastfeed for 3 months after the dose of KRINTAFEL [see Contraindications (4), Warnings and Precautions (5.2), Use in Specific Populations (8.2)].

Methemoglobinemia

Inform patients that methemoglobinemia has occurred with KRINTAFEL. Advise patients of the symptoms of methemoglobinemia and instruct them to seek medical advice promptly if such symptoms occur [see Warnings and Precautions (5.3)].

Psychiatric Symptoms

Advise patients with a history of psychiatric illness regarding the potential for new or worsening psychiatric symptoms with KRINTAFEL and instruct them to seek medical advice promptly if such symptoms occur [see Warnings and Precautions (5.4)].

Hypersensitivity Reactions

Inform patients that hypersensitivity reactions have occurred with KRINTAFEL. Advise patients of the symptoms of hypersensitivity reactions and instruct them to seek medical advice promptly if such symptoms occur [see Warnings and Precautions (5.5)].

Trademarks are owned by or licensed to the GSK group of companies.

GlaxoSmithKline

Durham, NC 27701

©2023 GSK group of companies or its licensor.

KFL:4PI

PATIENT INFORMATION

_ _ _ _ _ _ _ _ _ _ _ _ _ _ _ _ _ _ _ _ _ _ _ _ _ _ _ _ _ _ _ _ _ _ _ _ _ _ _ _ _ _ _ _ _ _ _ _ _ _ _ _ _

PHARMACIST—DETACH HERE AND GIVE PATIENT INFORMATION TO PATIENT

_ _ _ _ _ _ _ _ _ _ _ _ _ _ _ _ _ _ _ _ _ _ _ _ _ _ _ _ _ _ _ _ _ _ _ _ _ _ _ _ _ _ _ _ _ _ _ _ _ _ _ _ _

PATIENT INFORMATION

KRINTAFEL (KRIN-TAH-FELL)

(tafenoquine)
tablets, for oral use

What is KRINTAFEL?

- KRINTAFEL is a prescription medicine used to treat malaria caused by a parasite called Plasmodium vivax in patients aged 16 years and older who are also receiving chloroquine to treat acute Plasmodium vivax malaria.
- Malaria is a serious disease of the blood that is spread by infected mosquitos. KRINTAFEL does not work for all types of malaria.
- It is not known if KRINTAFEL is safe and effective in children younger than 16 years.

Do not use KRINTAFEL if you:

- have a blood problem called glucose-6-phosphate dehydrogenase (G6PD) deficiency (sometimes known as favism) or you have not been tested for G6PD deficiency. KRINTAFEL can cause a breakdown of red blood cells (hemolysis) in people with G6PD deficiency. Your healthcare provider will test you for G6PD deficiency before you start taking KRINTAFEL.
- are breastfeeding a child known to have G6PD deficiency or breastfeeding a child that has not been tested for G6PD deficiency.
- are allergic to tafenoquine or any of the ingredients in KRINTAFEL or if you have had an allergic reaction to similar medicines containing 8-aminoquinolines. See the end of this Patient Information leaflet for a complete list of ingredients in KRINTAFEL.

Before taking KRINTAFEL, tell your healthcare provider about all of your medical conditions, including if you:

- have or have had mental health problems.
- are pregnant or plan to become pregnant. KRINTAFEL can harm an unborn baby who has G6PD deficiency.
- are breastfeeding or plan to breastfeed. It is not known if KRINTAFEL passes into breast milk.

○ See “Do not use KRINTAFEL if you:”
○ Your healthcare provider should check your child for G6PD deficiency before you start breastfeeding.
○ If you know your child has G6PD deficiency, do not breastfeed while taking KRINTAFEL and for 3 months after your last dose of KRINTAFEL.

- Tell your healthcare provider about all the medicines you take, including prescription and over-the-counter medicines, vitamins, and herbal supplements. KRINTAFEL and other medicines may affect each other causing side effects.

How should I take KRINTAFEL?

- Your healthcare provider will test you for G6PD deficiency before you start taking KRINTAFEL.
- KRINTAFEL is given as 2 tablets that you take together as a single dose.
- You will take KRINTAFEL on the first or second day of your treatment with chloroquine.
- Take KRINTAFEL with food to make sure the right amount of medicine is absorbed into your body.
- Swallow KRINTAFEL tablets whole. Do not break, crush, or chew the tablets.
- If you vomit within 1 hour of taking KRINTAFEL, call your healthcare provider as you may need to take a second dose of KRINTAFEL.

What are the possible side effects of KRINTAFEL?

KRINTAFEL can cause serious side effects, including:

- Breakdown of red blood cells (hemolytic anemia). Contact your healthcare provider if you develop signs of hemolytic anemia, which include darkening of the lips or urine, dizziness, confusion, feeling tired, light-headedness, or shortness of breath.
- Hemolytic anemia in an unborn baby who has G6PD deficiency.

○ Females who are able to become pregnant should avoid pregnancy or use effective birth control (contraception) for 3 months after the dose of KRINTAFEL. Talk with your healthcare provider about birth control methods that might be right for you.

○ Your healthcare provider will do a pregnancy test before you start taking KRINTAFEL. Tell your healthcare provider right away if you become pregnant or think you might be pregnant during treatment with KRINTAFEL.

- Decrease of oxygen in your blood caused by a certain type of abnormal red blood cell (methemoglobinemia). Get medical help right away if you have darkening of the urine, nail beds, lips, or the inside of your mouth.
- Allergic (hypersensitivity) reactions. Serious allergic reactions can happen after you take KRINTAFEL. Allergic reactions can sometimes happen hours or days after you take a dose of KRINTAFEL. Tell your healthcare provider or get emergency help right away if you have any signs or symptoms of an allergic reaction including:

○ swelling of your face, lips, tongue, or throat
○ itching
○ trouble breathing

○ fainting, dizziness, feeling lightheaded
○ rash
○ hives

Other side effects of KRINTAFEL include mental health (psychiatric) symptoms. KRINTAFEL can cause new psychiatric symptoms including anxiety, abnormal dreams, and trouble sleeping (insomnia), or make the symptoms you already have worse. Contact your healthcare provider right away if you have new or worsening psychiatric symptoms.

The most common side effects of KRINTAFEL include: dizziness, nausea, vomiting, headache, and changes in laboratory tests for hemoglobin.

These are not all the possible side effects of KRINTAFEL.

Call your doctor for medical advice about side effects. You may report side effects to FDA at 1-800-FDA-1088.

Keep KRINTAFEL and all medicines out of the reach of children.

General information about the safe and effective use of KRINTAFEL.

Medicines are sometimes prescribed for purposes other than those listed in a Patient Information leaflet.

Do not use KRINTAFEL for a condition for which it was not prescribed. Do not give KRINTAFEL to other people even if they have the same symptoms that you have. It may harm them.

You can ask your pharmacist or healthcare provider for information about KRINTAFEL that is written for health professionals.

What are the ingredients in KRINTAFEL?

Active Ingredient: tafenoquine succinate.

Inactive Ingredients: magnesium stearate, mannitol, and microcrystalline cellulose.

GlaxoSmithKline, Durham, NC 27701

Trademarks are owned by or licensed to the GSK group of companies.

©2023 GSK group of companies or its licensor.

KFL:3PIL

For more information, call GlaxoSmithKline (GSK) at 1-888-825-5249.

This Patient Information has been approved by the U.S. Food and Drug Administration. Approved: August 2023

PACKAGE LABEL

PRINCIPAL DISPLAY PANEL

NDC 0173-0889-39

Krintafel

(tafenoquine)

tablets

150 mg

Rx Only

Patients must be tested for glucose-6-phosphate dehydrogenase deficiency before taking this medicine.

2 tablets to be taken as a single one-time dose

2 Tablets

GSK

Each tablet contains 150 mg of tafenoquine (equivalent to 188.2 mg tafenoquine succinate).

See prescribing information for dosage information.

Store at 20°C to 25°C (68°F to 77°F); excursions permitted to 15°C to 30°C (59°F to 86°F) [See USP controlled Room Temperature].

Store in original package. Protect from moisture. Do not remove desiccant.

Do not break or crush the tablets.

Do not accept if membrane seal under cap is missing or broken.

Manufactured by:

GlaxoSmithKline

Durham, NC 27701

Made in India

62000000090897 (A090897)